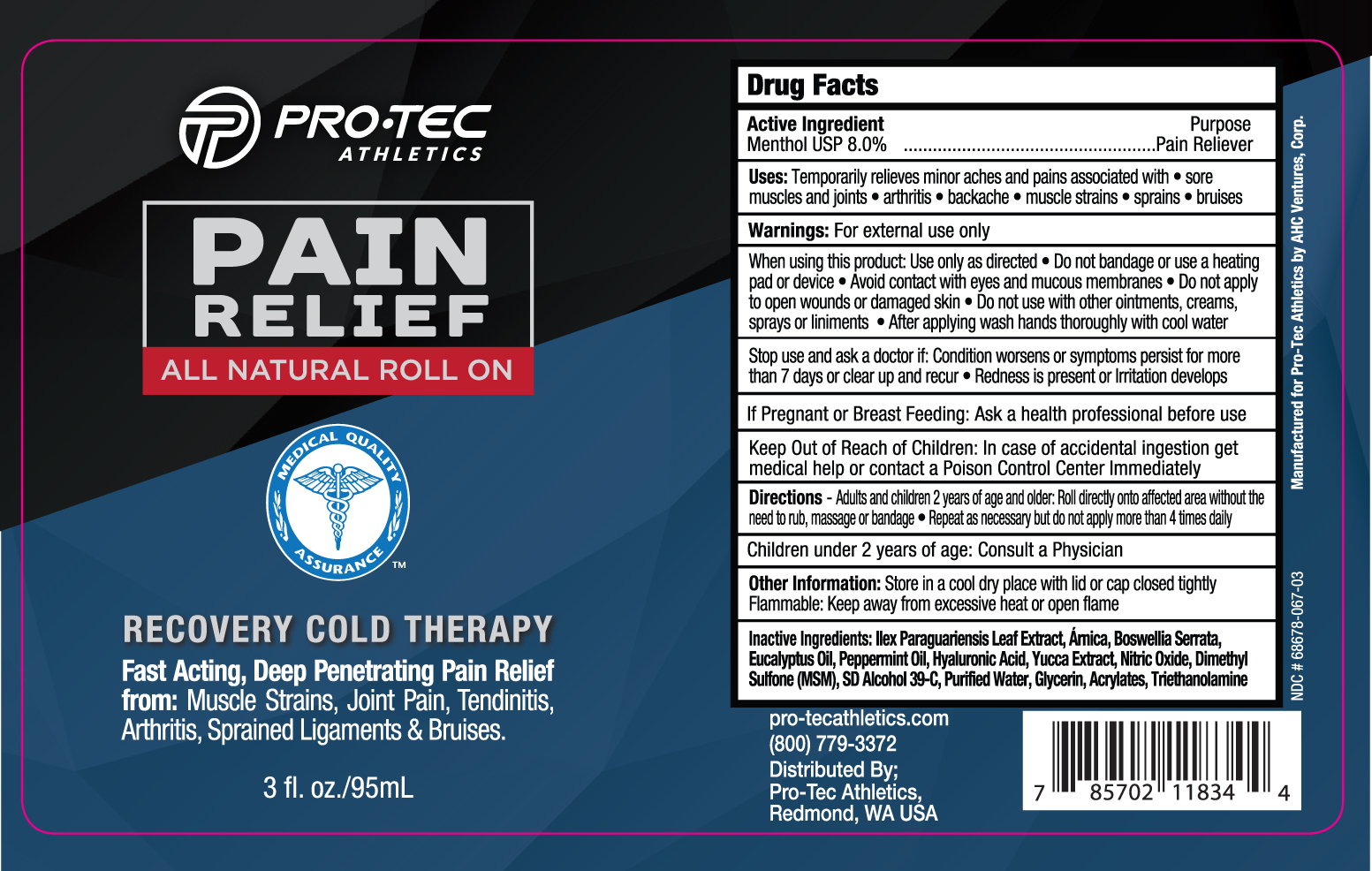 DRUG LABEL: PROTEC ROLL-ON
NDC: 68678-067 | Form: GEL
Manufacturer: ACH VENTURES CORP
Category: otc | Type: HUMAN OTC DRUG LABEL
Date: 20160224

ACTIVE INGREDIENTS: MENTHOL 8 g/100 mL
INACTIVE INGREDIENTS: ALCOHOL 50 mL/100 mL; WATER 26.99 mL/100 mL; ILEX PARAGUARIENSIS LEAF 5 mL/100 mL; DIMETHYL SULFONE 3 mL/100 mL; GLYCERIN 3 mL/100 mL; BOSWELLIA SERRATA WHOLE 1 mL/100 mL; ARNICA MONTANA 1 mL/100 mL; (C10-C30)ALKYL METHACRYLATE ESTER .40 mL/100 mL; TROLAMINE .40 mL/100 mL; YUCCA SCHIDIGERA .10 mL/100 mL; PEPPERMINT OIL .05 mL/100 mL; EUCALYPTUS OIL .05 mL/100 mL; NITRIC OXIDE .001 mL/100 mL

Active Ingredient

Menthol USP 8.0%

Purpose

Pain Reliever

Uses

Temporary relieves minor aches and pains associated with
•sore muscles and joints
•arthritis
•backache
•muscle strains
•sprains
•bruises

Warnings:

For external use only

When using this product: Use only as directed

•Do not bandage or use a heating pd or device
•Avoid contact with eyes and mucous membranes
•Do not apply to open wounds or damaged skin
•Do not use with other ointments, creams, sprays, liniments
•After applying wash hands thoroughly with cool water

Stop use and ask doctor if:

•condition worsens or symptoms persist for more than 7 days or clear up and recur
•Redness is present or irritation develops

If Pregnant or Breast Feeding:

Ask a health professional before use

Keep Out of Reach of Children

In case of accidental ingestion get medical help or contact a Poison Control Center Immediately

Directions

Adults and children 2 years of age and older: Roll directly onto affected area without the need to rub, massage or bandage. Repeat as necessary but do not apply more the 4 times daily

Children under 2 years of age: Consult a Physician

Other Information

Store in cool dry place with lid or cap closed tightly

Flammable: Keep away from excessive heat or open flame

Inactive Ingredients

Ilex Paraguariensis Leaf Extract, Arnica, Boswellia Serrata, Eucalyptus Oil, Peppermint Oil, Hyaluronic Acid, Yucca Extract, Nitric Oxide, Dimethyl Sulfone, SD Alcohol 39 C, Purified Water, Glycerin, Acrylates, Triethanolamine

PACKAGE LABEL

PRO.TEC ATHLETICS
PAIN RELIEF
ALL NATURAL ROLL ON
RECOVERY COLD THERAPY
Fast Acting, Deep Penetrating Pain Relief from: Muscle Strains, Joint Pain, Tendinitis, Arthritis, Sprained Ligaments & Bruises
3 fl.oz./95 mL